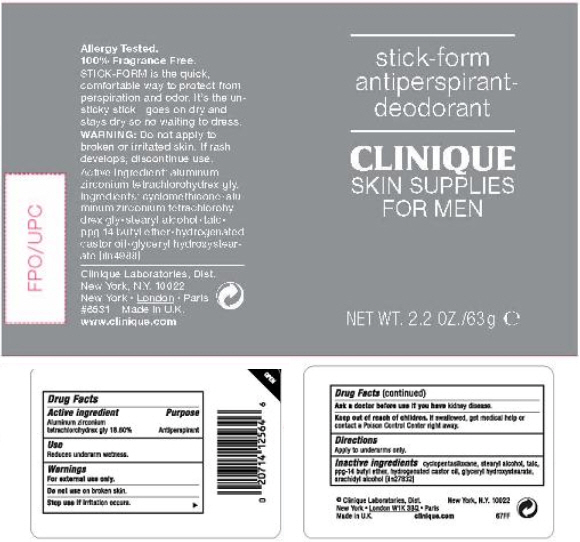 DRUG LABEL: SKIN SUPPLIES FOR MEN 
NDC: 49527-706 | Form: CREAM
Manufacturer: CLINIQUE LABORATORIES LLC
Category: otc | Type: HUMAN OTC DRUG LABEL
Date: 20210709

ACTIVE INGREDIENTS: ALUMINUM ZIRCONIUM TETRACHLOROHYDREX GLY 18.6 g/100 g
INACTIVE INGREDIENTS: CYCLOMETHICONE 5; STEARYL ALCOHOL; TALC; PPG-14 BUTYL ETHER; HYDROGENATED CASTOR OIL; ARACHIDYL ALCOHOL

SKIN SUPPLIES FOR MEN ANTIPERSPIRANT DEODORANT STICK

Active ingredient

Aluminum zirconium tetrachlorohydrex gly 18.60%

Purpose

Antiperspirant

Use

Reduces underarm wetness.

Warnings

For external use only.

Do not use on broken skin.

Stop use if irritation occurs.

Ask a doctor before use if you have kidney disease.

Keep out of reach of children. If swallowed, get medical help or contact a Poison Control Center right away.

Directions

Apply to underarms only.

Inactive ingredients

cyclopentasiloxane, stearyl alcohol, talc, ppg-14 butyl ether, hydrogenated castor oil, glyceryl hydroxystearate, arachidyl alcohol [iln27832]

PRINCIPAL DISPLAY PANEL - 63 g Cylinder Label

stick-form
antiperspirant-
deodorant

CLINIQUE
SKIN SUPPLIES
FOR MEN

NET WT. 2.2 OZ./63 g e